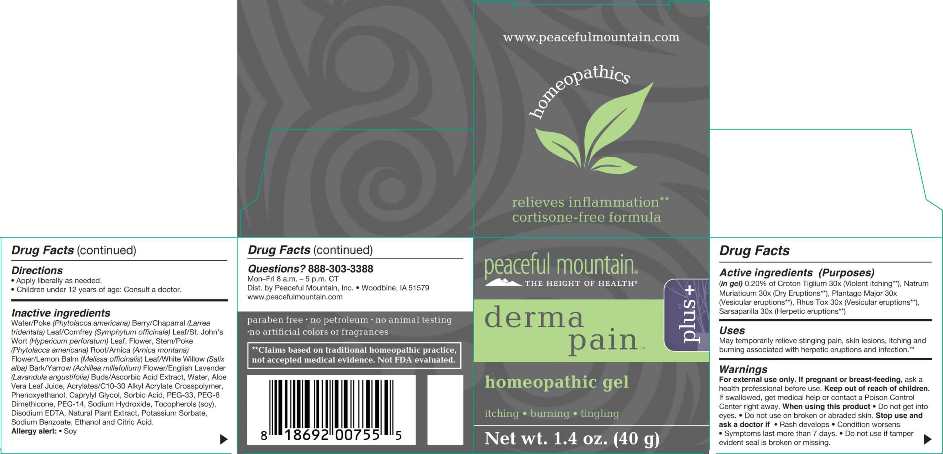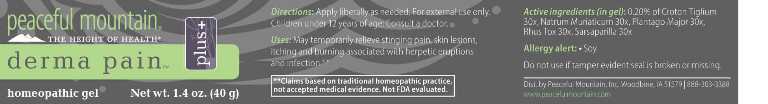 DRUG LABEL: Derma Pain Plus
NDC: 43846-0080 | Form: GEL
Manufacturer: Peaceful Mountain, Inc.
Category: homeopathic | Type: HUMAN OTC DRUG LABEL
Date: 20240613

ACTIVE INGREDIENTS: CROTON TIGLIUM SEED 30 [hp_X]/1 g; SODIUM CHLORIDE 30 [hp_X]/1 g; PLANTAGO MAJOR WHOLE 30 [hp_X]/1 g; TOXICODENDRON PUBESCENS LEAF 30 [hp_X]/1 g; SMILAX ORNATA ROOT 30 [hp_X]/1 g
INACTIVE INGREDIENTS: WATER; PHYTOLACCA AMERICANA FRUIT; ALOE VERA LEAF; PHENOXYETHANOL; CAPRYLYL GLYCOL; SORBIC ACID; CARBOMER INTERPOLYMER TYPE A (ALLYL SUCROSE CROSSLINKED); POLYETHYLENE GLYCOL 1600; PEG-8 DIMETHICONE; POLYETHYLENE GLYCOL 700; LARREA TRIDENTATA LEAF; COMFREY LEAF; HYPERICUM PERFORATUM; PHYTOLACCA AMERICANA ROOT; ARNICA MONTANA FLOWER; MELISSA OFFICINALIS LEAF; SALIX ALBA BARK; ACHILLEA MILLEFOLIUM FLOWER; SODIUM HYDROXIDE; LAVANDULA ANGUSTIFOLIA SUBSP. ANGUSTIFOLIA FLOWER; ASCORBIC ACID; .ALPHA.-TOCOPHEROL; EDETATE DISODIUM; OREGANO; POTASSIUM SORBATE; SODIUM BENZOATE; ALCOHOL; CITRIC ACID MONOHYDRATE

DRUG FACTS:

ACTIVE INGREDIENTS:

(in gel): 0.20% of Croton Tiglium 30X, Natrum Muriaticum 30X, Plantago Major 30X, Rhus Tox 30X, Sarsaparilla 30X.

INDICATIONS:

May temporarily relieve stinging pain, skin lesions, itching and burning associated with herpetic eruptions and infection.**

**Claims based on traditional homeopathic practice, not accepted medical evidence. Not FDA evaluated.

WARNINGS:

For external use only.

If pregnant or breast-feeding, ask a health professional before use.

Keep out of reach of children. If swallowed, get medical help or contact a Poison Control Center right away.

When using this product • Do not get into eyes. • Do not use on broken or abraded skin.

Stop use and ask a doctor if • Rash develops Condition worsens • Symptoms last more than 7 days. • Do not use if tamper evident seal is broken or missing.

Keep out of reach of children. If swallowed, get medical help or contact a Poison Control Center right away.

DIRECTIONS:

• Apply liberally as needed.

• Children under 12 years of age: Consult a doctor.

INDICATIONS:

May temporarily relieve stinging pain, skin lesions, itching and burning associated with herpetic eruptions and infection.**

**Claims based on traditional homeopathic practice, not accepted medical evidence. Not FDA evaluated.

INACTIVE INGREDIENTS:

Purified Water, Poke (Berries) Phytolacca Americana, Aloe Vera Leaf Juice, Phenoxyethanol, Caprylyl Glycol, Sorbic Acid, Acrylates/C10-30 Alkyl Acrylate Crosspolymer, PEG-33, PEG-8 Dimethicone, PEG-14, Chaparral (Leaf) Larrea Tridentata, Comfrey (Leaf) Symphytum Officinale, St. John's Wart (Leaf, Flower, Stem) Hypericum Perforatum, Poke (Root) Phytolacca Americana, Arnica (Flower) Arnica Montana, Lemon Balm (Leaf) Melissa Officinalis, White Willow (Bark) Salix Alba, Yarrow (Flower) Achillea Millefolium, Sodium Hydroxide, English Lavender (Buds) Lavandula Angustifolia, Ascorbic Acid (Vitamin C), Tocopherols (Vitamin E), Edetate Disodium (EDTA), Natural Plant Extract (Origanox WS), Potassium Sorbate, Sodium Benzoate, Ethanol, Citric Acid.
Allergy Alert • Soy

QUESTIONS:

888-303-3388

Mon-Fri 8a.m-5p.m CST

Dist. by Peaceful Mountain, Inc. Woodbine, IA 51579

www.peacefulmountain.com

PACKAGE LABEL DISPLAY:

peaceful mountain
THE HEIGHT OF HEALTH
derma pain plus+
homeopathic gel
Net wt. 1.4 oz. (40 g)